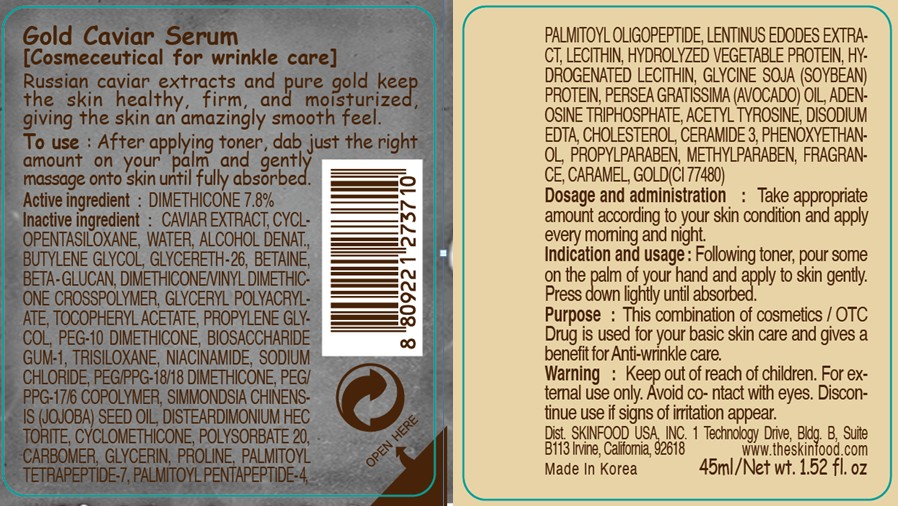 DRUG LABEL: GOLD CAVIAR SERUM
NDC: 76214-010 | Form: CREAM
Manufacturer: SKINFOOD CO., LTD.
Category: otc | Type: HUMAN OTC DRUG LABEL
Date: 20110727

ACTIVE INGREDIENTS: DIMETHICONE 3.51 mL/45 mL
INACTIVE INGREDIENTS: CAVIAR; CYCLOMETHICONE 5; WATER; BUTYLENE GLYCOL; GLYCERETH-26; BETAINE; PROPYLENE GLYCOL; BIOSACCHARIDE GUM-1; TRISILOXANE; NIACINAMIDE; SODIUM CHLORIDE; JOJOBA OIL; CYCLOMETHICONE; POLYSORBATE 20; PHENOXYETHANOL; GLYCERIN; PROPYLPARABEN; PROLINE; PALMITOYL TETRAPEPTIDE-7; PALMITOYL PENTAPEPTIDE-4; METHYLPARABEN; LECITHIN, SOYBEAN; HYDROGENATED SOYBEAN LECITHIN; SOYBEAN; PERSEA AMERICANA VAR. AMERICANA LEAF; ADENOSINE TRIPHOSPHATE; ADENOSINE; EDETATE DISODIUM; CHOLESTEROL; GOLD; CERAMIDE 3; CARAMEL

Drug Facts

Active ingredient: DIMETHICONE 7.8%

Inactive ingredients:

CAVIAR EXTRACT, CYCLOPENTASILOXANE, WATER, ALCOHOL DENAT., BUTYLENE GLYCOL, GLYCERETH-26, BETAINE, BETA-GLUCAN, DIMETHICONE/VINYL DIMETHICONE CROSSPOLYMER, GLYCERYL POLYACRYLATE, TOCOPHERYL ACETATE, PROPYLENE GLYCOL, PEG-10 DIMETHICONE, BIOSACCHARIDE GUM-1, TRISILOXANE, NIACINAMIDE, SODIUM CHLORIDE, PEG/PPG-18/18 DIMETHICONE, PEG/PPG-17/6 COPOLYMER, SIMMONDSIA CHINENSIS (JOJOBA) SEED OIL, DISTEARDIMONIUM HECTORITE, CYCLOMETHICONE, POLYSORBATE 20, CARBOMER, GLYCERIN, PROLINE, PALMITOYL TETRAPEPTIDE-7, PALMITOYL PENTAPEPTIDE-4, PALMITOYL OLIGOPEPTIDE, LENTINUS EDODES EXTRACT, LECITHIN, HYDROLYZED VEGETABLE PROTEIN, HYDROGENATED LECITHIN, GLYCINE SOJA (SOYBEAN) PROTEIN, PERSEA GRATISSIMA (AVOCADO) OIL, ADENOSINE TRIPHOSPHATE, ACETYL TYROSINE, ADENOSINE, DISODIUM EDTA, CHOLESTEROL, CERAMIDE 3, PHENOXYETHANOL, PROPYLPARABEN, METHYLPARABEN, FRAGRANCE, CARAMEL, GOLD

Purpose:

This combination of cosmetics is used for your basic skin care and gives a benefit for Anti-wrinkle care.

Warnings:

For external use only. Avoid contact with eyes. Discontinue use if signs of irritation appear.

Keep out of reach of children:

Keep out of reach of children.

Indication and usage:

Following toner, pour some on the palm of your hand and apply to skin gently. Press down lightly until absorbed.

Dosage and administration:

Take appropriate amount according to your skin condition and apply every morning and night.